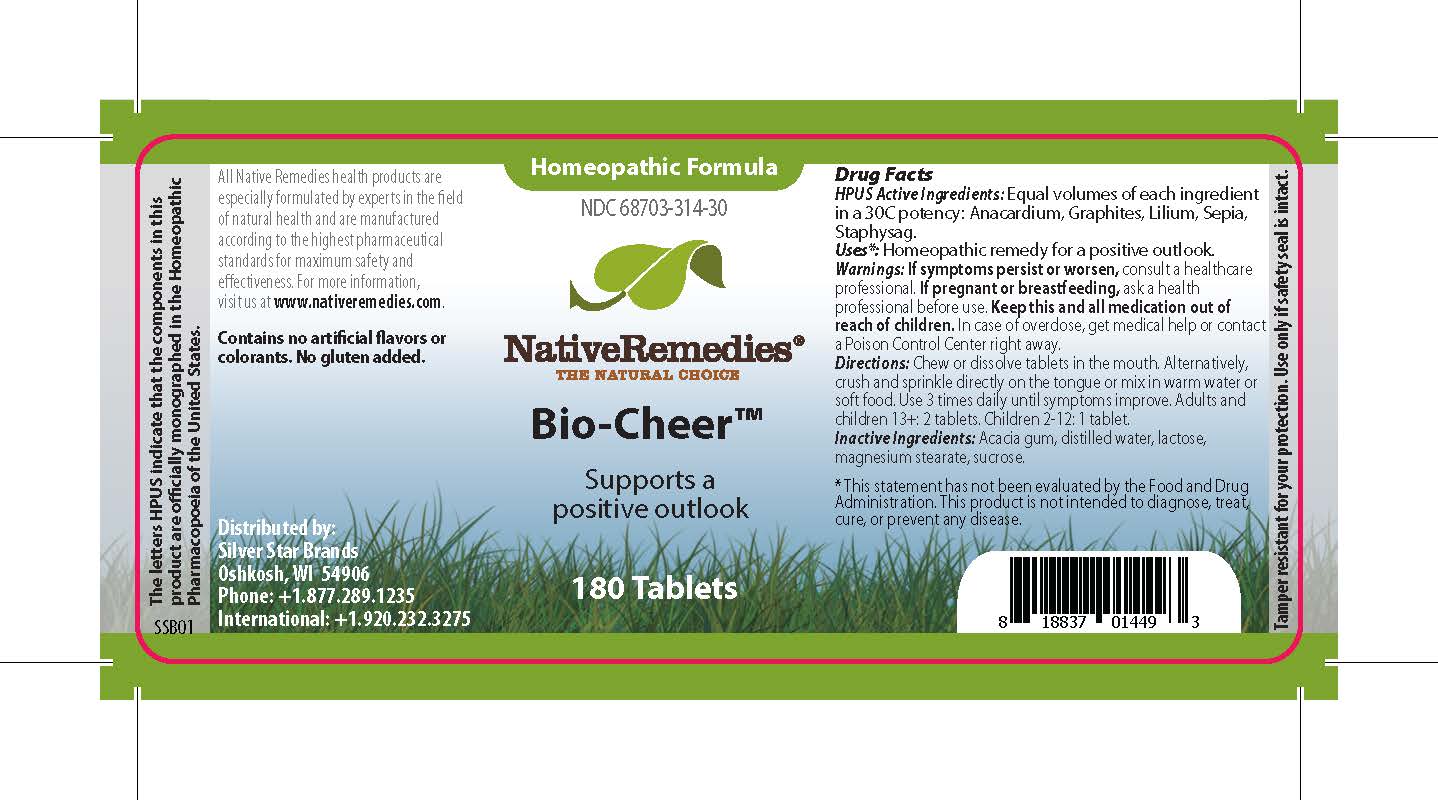 DRUG LABEL: Bio-Cheer
NDC: 68703-314 | Form: TABLET
Manufacturer: Silver Star Brands
Category: homeopathic | Type: HUMAN OTC DRUG LABEL
Date: 20250101

ACTIVE INGREDIENTS: GRAPHITE 30 [hp_C]/1 1; DELPHINIUM STAPHISAGRIA WHOLE 30 [hp_C]/1 1; ANACARDIUM OCCIDENTALE FRUIT 30 [hp_C]/1 1; LILIUM LANCIFOLIUM WHOLE 30 [hp_C]/1 1; SEPIA OFFICINALIS JUICE 30 [hp_C]/1 1
INACTIVE INGREDIENTS: WATER; SUCROSE; MAGNESIUM STEARATE; ACACIA; LACTOSE, UNSPECIFIED FORM

NativeRemedies® Bio-Cheer™

HPUS Active Ingredients: Equal volumes of each ingredient in a 30C potency: Anacardium, Graphites, Lilium, Sepia, Staphysag.

The letters HPUS indicate that the components in this product are officially monographed in the Homoeopathic Pharmacopoeia of the United States.

Uses*

Uses*: Homeopathic remedy for a positive outlook.

*This statement has not been evaluated by the Food and Drug Admininstration. This product is not intended to diagnose, treat, cure, or prevent any disease.

Warnings

If symptoms persist or worsen, consult a healthcare professional. If pregnant or breastfeeding, ask a health professional before use. Keep this and all medication out of reach of children. In case of overdose, get medical help or contact a Poison Control Center right away.

Directions

Chew or dissolve tablets in the mouth. Alternatively, crush and sprinkle directly on the tongue or mix in warm water or soft food. Use 3 times daily until symptoms improve. Adults and children 13+: 2 tablets. Children 2-12: 1 tablet.

OTHER SAFETY INFORMATION

Contains no artificial flavors or colorants. No gluten added.

Tamper resistant for your protection. Use only if safety seal is intact.

Inactive Ingredients

Acacia gum, distilled water, lactose, magnesium stearate, sucrose.

KEEP OUT OF REACH OF CHILDREN

Keep this and all medication out of reach of children.

PREGNANCY OR BREAST FEEDING

If pregnant or breastfeeding, ask a health professional before use.

PURPOSE

Supports a positive outlook.